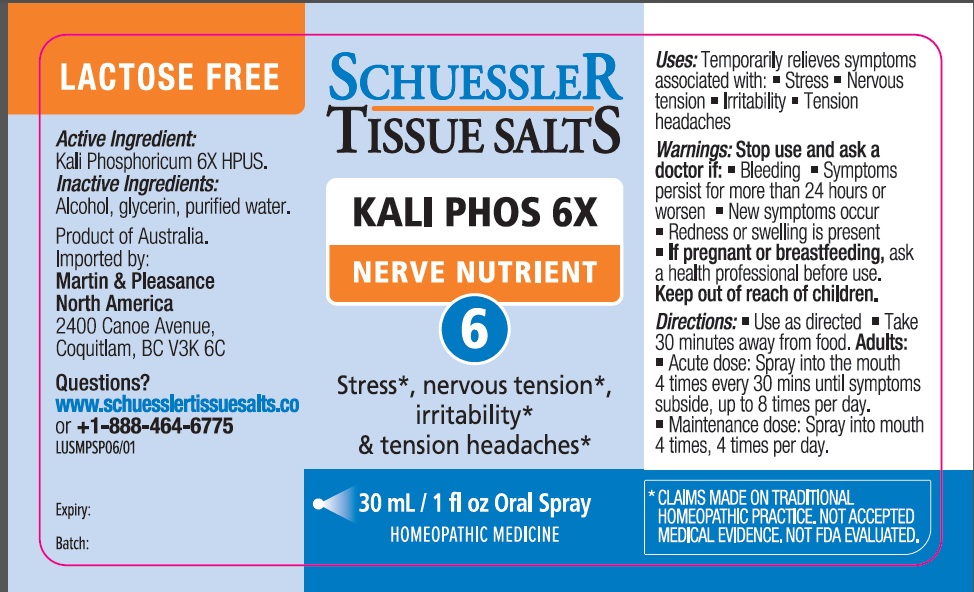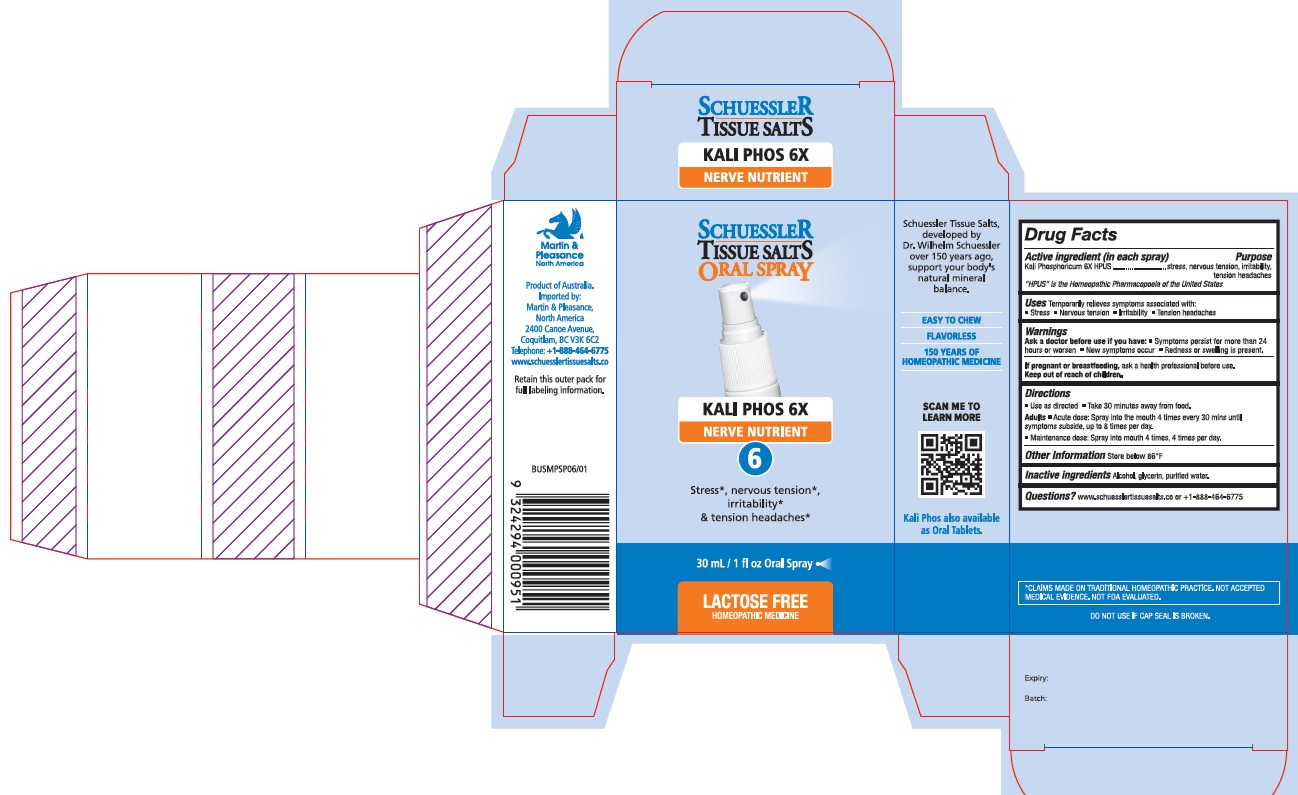 DRUG LABEL: Schuessler Tissue Salts Kali Phos Nerve Nutrient 6
NDC: 84999-006 | Form: SPRAY
Manufacturer: Martin & Pleasance Pty Ltd
Category: homeopathic | Type: HUMAN OTC DRUG LABEL
Date: 20250701

ACTIVE INGREDIENTS: DIBASIC POTASSIUM PHOSPHATE 6 [hp_X]/30 mL
INACTIVE INGREDIENTS: ALCOHOL; GLYCERIN; WATER

Active Ingredients (in each spray) Purpose

Kali Phosphoricum 6X HPUS stress, nervous tension, irritability, tension headaches

" HPUS" is the Homeopathic Pharmacopoeia of the United States

Uses

- Temporarily relieves symptoms associated with:
- Stress
- Nervous tension
- Irritability
- Tension headaches

Warnings

Ask a doctor before usa if you have:

- Symptoms persist for more than 24 hours or worsen
- New symptoms occur
- Redness or swelling is present.

If pregnant or breastfeeding, ask a health professional before use. Keep out of reach of children.

Directions

- Use as directed
- Take 30 minutes away from food.

Adults

- Acute dose: Spray into the mouth 4 times every 30 mins until symptoms subside, up to 8 times per day.
- Maintenance dose: Spray into mouth 4 times, 4 times per day.

Other Information

Store below 86°F

Inactive Ingredients

Alcohol , Glycerin, water

Questions?www.schuesslertissuesalts.co or + 1-888-464-6775